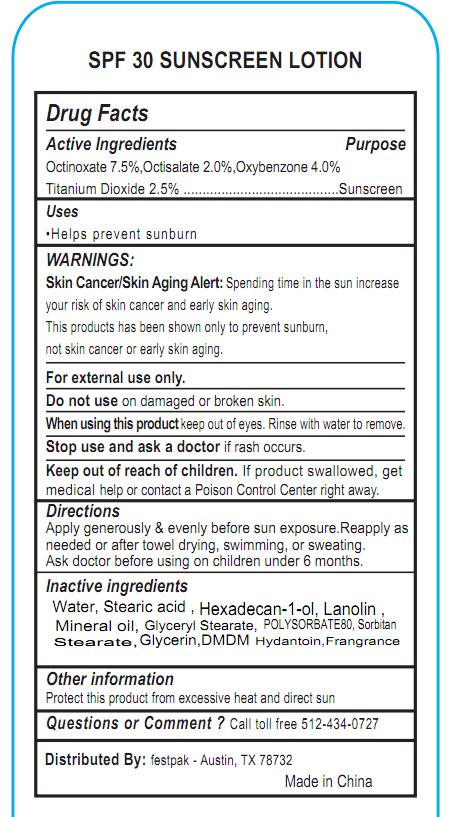 DRUG LABEL: Sunscreen
NDC: 71011-004 | Form: LOTION
Manufacturer: NingBo Huize Commodity Co.,Ltd.
Category: otc | Type: HUMAN OTC DRUG LABEL
Date: 20180718

ACTIVE INGREDIENTS: OXYBENZONE 4 g/100 g; OCTISALATE 2 g/100 g; OCTINOXATE 7.5 g/100 g
INACTIVE INGREDIENTS: GLYCERIN; LANOLIN; DMDM HYDANTOIN; WATER; STEARIC ACID; HEXADECANAL; MINERAL OIL

71011-004 sunscreen

Active Ingredients

Octinoxate 7.5%,Octisalate 2.0%,Oxybenzone 4.0%

Purpose

Sunscreen

Uses

Helps prevent sunburn

WARNINGS:

Skin Cancer/Skin Aging Alert: Spending time in the sun increase your risk of skin cancer and early skin aging. This products has been shown only to prevent sunburn, not skin cancer or early skin aging. For external use only. Do not use on damaged or broken skin. When using this product keep out of eyes. Rinse with water to remove. Stop use and ask a doctor if rash occurs

Keep out of reach of children.

If product swallowed, get medical help or contact a Poison Control Center right away.

Directions

Apply generously & evenly before sun exposure.Reapply as needed or after towel drying, swimming, or sweating. Ask doctor before using on children under 6 months.

Inactive ingredients

Water, Stearic acid , Hexadecan-1-ol, Lanolin , Mineral oil, Glyceryl Stearate, POLYSORBATE80, Sorbitan Stearate,Glycerin,DMDM Hydantoin,Frangrance